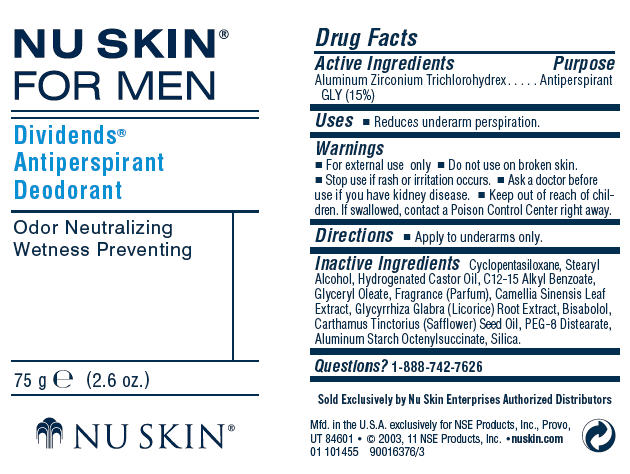 DRUG LABEL: Dividends
NDC: 62839-1455 | Form: STICK
Manufacturer: NSE Products, Inc.
Category: otc | Type: HUMAN OTC DRUG LABEL
Date: 20110627

ACTIVE INGREDIENTS: Aluminum Zirconium Trichlorohydrex Gly 20 g/100 g
INACTIVE INGREDIENTS: Cyclomethicone 5; Stearyl Alcohol; Hydrogenated Castor Oil; Alkyl (C12-15) Benzoate; Glyceryl Monooleate; Green Tea Leaf; Glycyrrhiza Glabra; Levomenol; Safflower Oil; PEG-8 Distearate; Aluminum Starch Octenylsuccinate; Silicon Dioxide

NU SKIN®
FOR MEN
Dividends®
Antiperspirant
Deodorant

Drug Facts

Active Ingredients

Aluminum Zirconium Trichlorohydrex GLY (15%)

Purpose

Antiperspirant

Uses

- Reduces underarm perspiration.

Warnings

- For external use only

- Do not use on broken skin.

- Stop use if rash or irritation occurs.

- Ask a doctor before use if you have kidney disease.

- Keep out of reach of children. If swallowed, contact a Poison Control Center right away.

Directions

- Apply to underarms only.

Inactive Ingredients

Cyclopentasiloxane, Stearyl Alcohol, Hydrogenated Castor Oil, C12-15 Alkyl Benzoate, Glyceryl Oleate, Fragrance (Parfum), Camellia Sinensis Leaf Extract, Glycyrrhiza Glabra (Licorice) Root Extract, Bisabolol, Carthamus Tinctorius (Safflower) Seed Oil, PEG-8 Distearate, Aluminum Starch Octenylsuccinate, Silica.

Questions?

1-888-742-7626

Mfd. in the U.S.A. exclusively for NSE Products, Inc., Provo, UT 84601

PRINCIPAL DISPLAY PANEL - 75 g Container Label

NU SKIN®
FOR MEN

Dividends®
Antiperspirant
Deodorant

Odor Neutralizing
Wetness Preventing

75 g e (2.6 oz.)

NU SKIN®